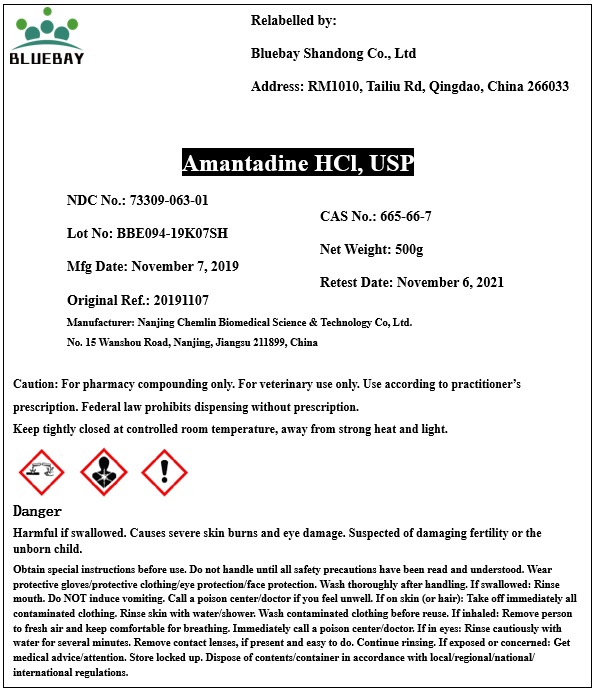 DRUG LABEL: Amantadine Hydrochloride
NDC: 73309-063 | Form: POWDER
Manufacturer: BLUEBAY SHANDONG CO.,LTD
Category: other | Type: BULK INGREDIENT
Date: 20191202

ACTIVE INGREDIENTS: AMANTADINE HYDROCHLORIDE 1 g/1 g

Amantadine hydrochloride